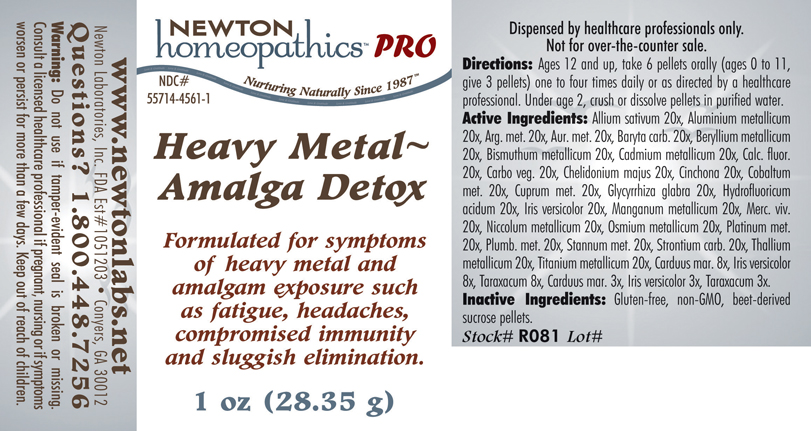 DRUG LABEL: Heavy Metal - Amalga Detox 
NDC: 55714-4561 | Form: PELLET
Manufacturer: Newton Laboratories, Inc.
Category: homeopathic | Type: HUMAN PRESCRIPTION DRUG LABEL
Date: 20110601

ACTIVE INGREDIENTS: Garlic 20 [hp_X]/1 g; Aluminum 20 [hp_X]/1 g; Silver 20 [hp_X]/1 g; Gold 20 [hp_X]/1 g; Barium Carbonate 20 [hp_X]/1 g; Beryllium 20 [hp_X]/1 g; Bismuth 20 [hp_X]/1 g; Cadmium 20 [hp_X]/1 g; Calcium Fluoride 20 [hp_X]/1 g; Activated Charcoal 20 [hp_X]/1 g; Chelidonium Majus 20 [hp_X]/1 g; Cinchona Officinalis Bark 20 [hp_X]/1 g; Cobalt 20 [hp_X]/1 g; Copper 20 [hp_X]/1 g; Glycyrrhiza Glabra 20 [hp_X]/1 g; Hydrofluoric Acid 20 [hp_X]/1 g; Iris Versicolor Root 20 [hp_X]/1 g; Manganese 20 [hp_X]/1 g; Mercury 20 [hp_X]/1 g; Nickel 20 [hp_X]/1 g; Osmium 20 [hp_X]/1 g; Platinum 20 [hp_X]/1 g; Lead 20 [hp_X]/1 g; Tin 20 [hp_X]/1 g; Strontium Carbonate 20 [hp_X]/1 g; Thallium 20 [hp_X]/1 g; Titanium 20 [hp_X]/1 g; Silybum Marianum Seed 8 [hp_X]/1 g; Taraxacum Officinale 8 [hp_X]/1 g
INACTIVE INGREDIENTS: Sucrose

Heavy Metal - Amalga Detox

INDICATIONS & USAGE SECTION

Heavy Metal - Amalga Detox Formulated for symptoms of heavy metal and amalgam exposure such as fatigue, headaches, compromised immunity and sluggish elimination.

DOSAGE & ADMINISTRATION SECTION

Directions: Ages 12 and up, take 6 pellets orally (ages 0 to 11, give 3 pellets) one to four times daily or as directed by a healthcare professional. Under age 2, crush or dissolve pellets in purified water.

ACTIVE INGREDIENT SECTION

Allium sativum 20x, Aluminium metallicum 20x, Arg. met. 20x, Aur. met. 20x, Baryta carb. 20x, Beryllium metallicum 20x, Bismuthum metallicum 20x, Cadmium metallicum 20x, Calc. fluor. 20x, Carbo veg. 20x, Chelidonium majus 20x, Cinchona 20x, Cobaltum met. 20x, Cuprum met. 20x, Glycyrrhiza glabra 20x, Hydrofluoricum acidum 20x, Iris versicolor 20x, Manganum metallicum 20x, Merc. viv. 20x, Niccolum metallicum 20x, Osmium metallicum 20x, Platinum met. 20x, Plumb. met. 20x, Stannum met. 20x, Strontium carb. 20x, Thallium metallicum 20x, Titanium metallicum 20x, Carduus mar. 8x, Iris versicolor 8x, Taraxacum 8x, Carduus mar. 3x, Iris versicolor 3x, Taraxacum 3x.

PURPOSE SECTION

Formulated for symptoms of heavy metal and amalgam exposure such as fatigue, headaches, compromised immunity and sluggish elimination.

INACTIVE INGREDIENT SECTION

Inactive Ingredients: Gluten-free, non-GMO, beet-derived sucrose pellets.

QUESTIONS? SECTION

www.newtonlabs.net Newton Laboratories, Inc. FDA Est # 1051203 - Conyers, GA 30012
Questions? 1.800.448.7256

WARNINGS SECTION

Warning: Do not use if tamper - evident seal is broken or missing. Consult a licensed healthcare professional if pregnant, nursing or if symptoms worsen or persist for more than a few days. Keep out of reach of children.

PREGNANCY OR BREAST FEEDING SECTION

Consult a licensed healthcare professional if pregnant or nursing or if symptoms worsen or persist for more than a few days.

KEEP OUT OF REACH OF CHILDREN SECTION

Keep out of reach of children.